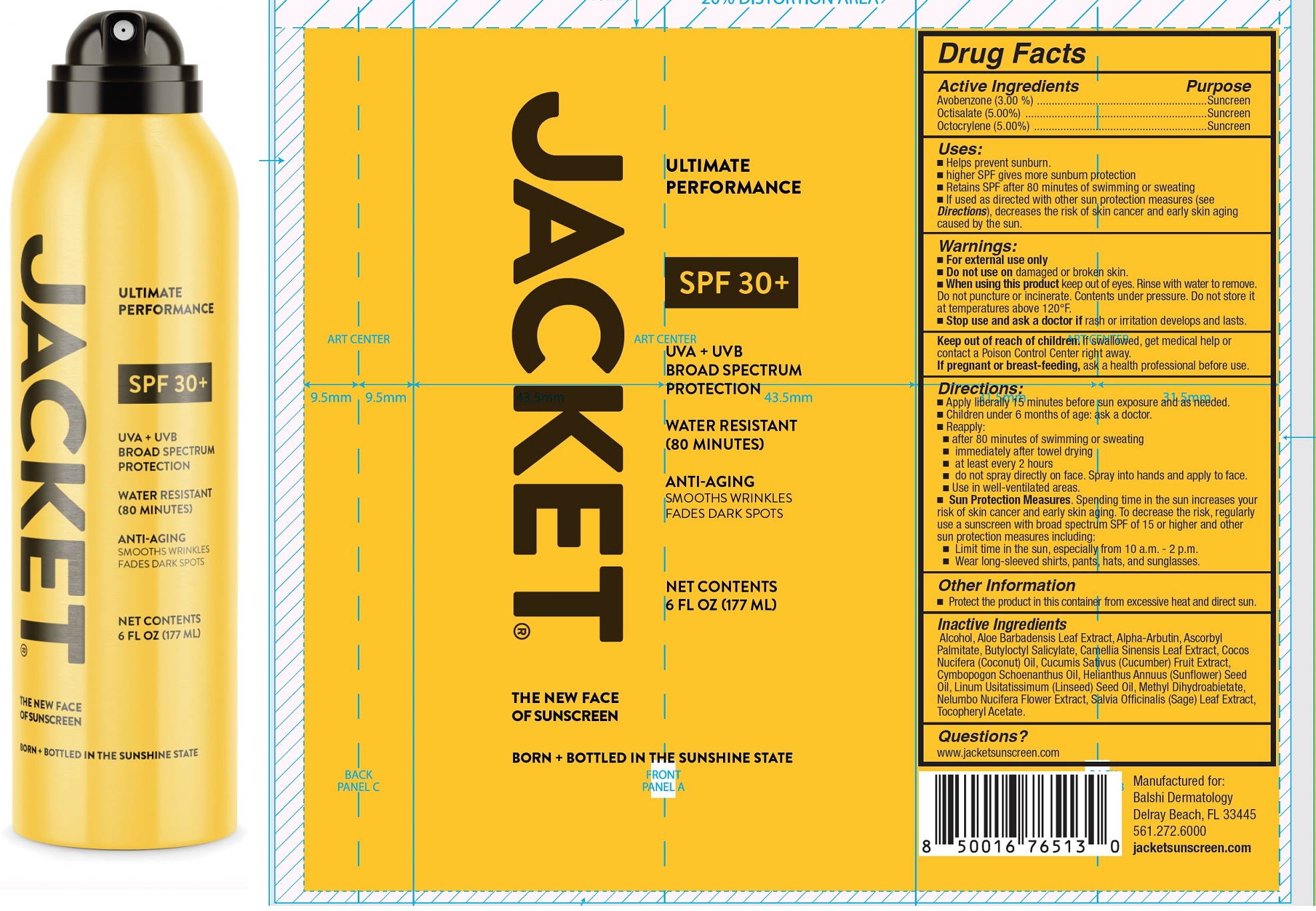 DRUG LABEL: Jacket Ultimate Performance Sunscreen SPF 30
NDC: 71070-599 | Form: LIQUID
Manufacturer: BALSHI MD DERMACEUTICALS
Category: otc | Type: HUMAN OTC DRUG LABEL
Date: 20250505

ACTIVE INGREDIENTS: AVOBENZONE 30 mg/1 mL; OCTISALATE 50 mg/1 mL; OCTOCRYLENE 50 mg/1 mL
INACTIVE INGREDIENTS: ALCOHOL; ALOE VERA LEAF; ALPHA-ARBUTIN; ASCORBYL PALMITATE; BUTYLOCTYL SALICYLATE; GREEN TEA LEAF; COCONUT OIL; CUCUMBER; CYMBOPOGON SCHOENANTHUS OIL; SUNFLOWER OIL; LINSEED OIL; METHYL DIHYDROABIETATE; NELUMBO NUCIFERA FLOWER; SAGE; .ALPHA.-TOCOPHEROL ACETATE

Jacket Ultimate Performance Sunscreen SPF 30+

Active Ingredients

Avobenzone (3.00%)
Octisalate (5.00%)
Octocrylene (5.00%)

Purpose

Sunscreen

Uses:

- Helps prevent sunburn.
- higher SPF gives more sunburn protection
- Retains SPF after 80 minutes of swimming or sweating
- If used as directed with other sun protection measures (see Directions), decreases the risk of skin cancer and early skin agingcaused by the sun.

Warnings:

- For external use only

Do not use

- on damaged or broken skin.

When using this product

- keep out of eyes. Rinse with water to remove.
- Do not puncture or incinerate. Contents under pressure. Do not store it at temperatures above 120°F.

Stop use and ask a doctor if

- rash or irritation develops and lasts.

Keep out of reach of children.

If swallowed, get medical help or contact a Poison Control Center right away.

If pregnant or breast-feeding,

ask a health professional before use.

Directions.

- Apply liberally 15 minutes before sun exposure and as needed.
- Children under 6 months of age: ask a doctor.
- Reapply:
- after 80 minutes of swimming or sweating
- immediately after towel drying
- at least every 2 hours
- do not spray directly on face. Spray into hands and apply to face.
- Use in well-ventilated areas.
- Sun Protection Measures.Spending time in the sun increase your risk of skin cancer and early skin aging. To decrease this risk, regularly use a sunscreen with a broad spectrum SPF of 15 or higher and other sun protection measures including:
- Limit time in the sun, especially from 10 a.m.-2p.m.
- Wear long-sleeved shirts, pants,hats,and sunglasses.

Other Information

- Protect the product in this container from excessive heat and direct sun.

Inactive Ingredients

Alcohol, Aloe Barbadensis Leaf Extract, Alpha-Arbutin, Ascorbyl Palmitate, Butyloctyl Salicylate, Camellia Sinensis Leaf Extract, Cocos Nucifera (Coconut) Oil, Cucumis Sativus (Cucumber) Fruit Extract, Cymbopogon Schoenanthus Oil, Helianthus Annuus (Sunflower) Seed Oil, Linum Usitatissimum (Linseed) Seed Oil, Methyl Dihydroabietate, Nelumbo Nucifera Flower Extract, Salvia Officinalis (Sage) Leaf Extract, Tocopheryl Acetate.

Questions?

www.jacketsunscreen.com